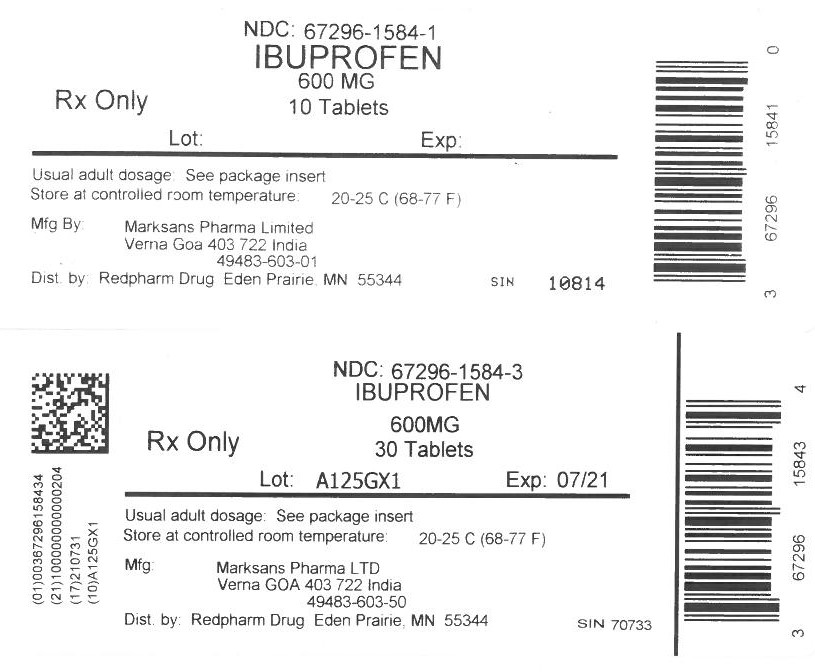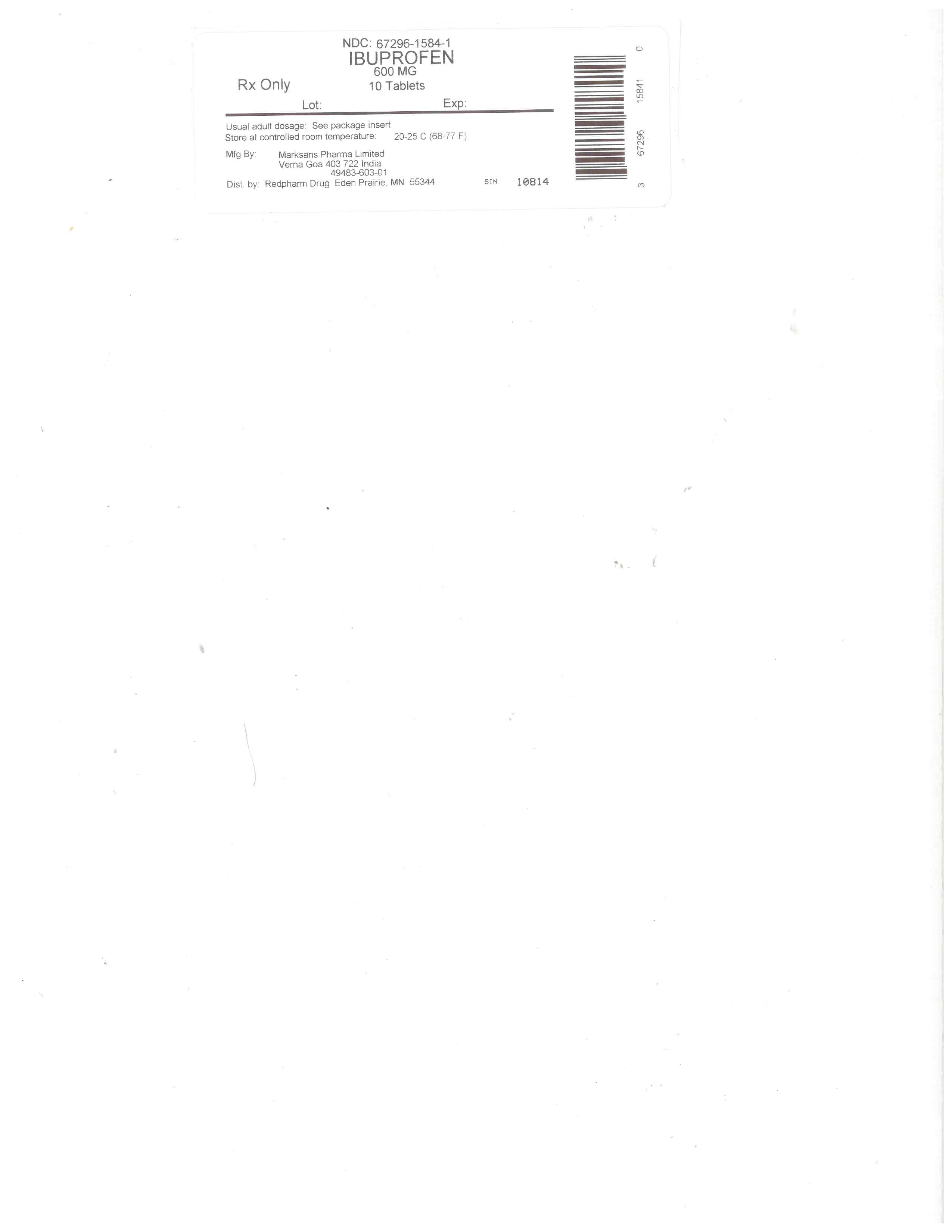 DRUG LABEL: IBUPROFEN
NDC: 67296-1584 | Form: TABLET, FILM COATED
Manufacturer: RedPharm Drug, Inc.
Category: prescription | Type: HUMAN PRESCRIPTION DRUG LABEL
Date: 20240815

ACTIVE INGREDIENTS: IBUPROFEN 600 mg/1 1
INACTIVE INGREDIENTS: MAGNESIUM STEARATE; CELLULOSE, MICROCRYSTALLINE; STARCH, PREGELATINIZED CORN; CROSCARMELLOSE SODIUM; POLYETHYLENE GLYCOL, UNSPECIFIED; POLYVINYL ALCOHOL, UNSPECIFIED; TITANIUM DIOXIDE; TALC; SILICON DIOXIDE

ibuprofen

HOW SUPPLIED

600mg (white to off white, capsule shaped, biconvex, film coated tablets debossed with '122' on one side and plain on the other side) Bottles of 30, 50, 100 & 500